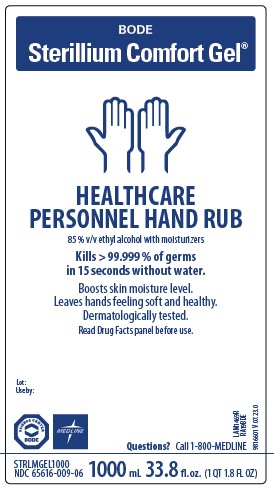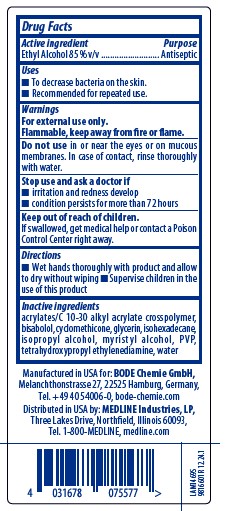 DRUG LABEL: Sterillium Comfort
NDC: 65616-009 | Form: GEL
Manufacturer: BODE Chemie GmbH
Category: otc | Type: HUMAN OTC DRUG LABEL
Date: 20250430

ACTIVE INGREDIENTS: ALCOHOL 85 mL/100 mL
INACTIVE INGREDIENTS: CYCLOMETHICONE; WATER; LEVOMENOL; GLYCERIN; ISOHEXADECANE; ISOPROPYL ALCOHOL; POVIDONE K90; EDETOL; CARBOMER INTERPOLYMER TYPE A (55000 CPS); MYRISTYL ALCOHOL

Sterillium Comfort Gel NDC 65616-009

Active ingredient

Ethyl Alcohol 85% v/v

Purpose

Antiseptic

Uses

- To decrease bacteria on the skin.
- Recommended for repeated use.

Warnings

For external use only.

Flammable, keep away from fire or flame.

DO NOT USE

Do not usein or near the eyes or on mucous membranes.

In case of contact, rinse thoroughly with water.

Stop use and ask a doctor if

- irritation and redness develop
- condition persists for more than 72 hours

Keep out of reach of children.

If swallowed, get medical help or contact a Poison Control Center right away.

Directions

- Wet hands thoroughly with product and allow to dry without wiping
- Supervise children in the use of this product

Inactive ingredients

Acrylates/C 10-30 Alkyl Acrylate Crosspolymer, Bisabolol, Cyclomethicone, Glycerin, Isohexadecane, Isopropyl Alcohol, Myristyl Alcohol, PVP, Tetrahydroxypropyl Ethylenediamine, Water.

Directions

- Wet hands thoroughly with product and allow to dry without wiping
- Supervise children in the use of this product

PACKAGE LABEL

BODE

Sterillium Comfort Gel

HEALTHCARE

PERSONNEL HAND RUB

85% v/v ethyl alcohol with moisturizers

Kills > 99.999% of germs

in 15 seconds without water.

Boosts skin moisture level.

Leaves hands feeling soft and healthy.

Dermatologically tested.

Read Drug Facts panel before use.

Lot:

Use by:

Questions? Call 1-800-MEDLINE

NDC 65616-009-06

1000 mL 33.8 fl.oz. (1QT 1.8 FL OZ)